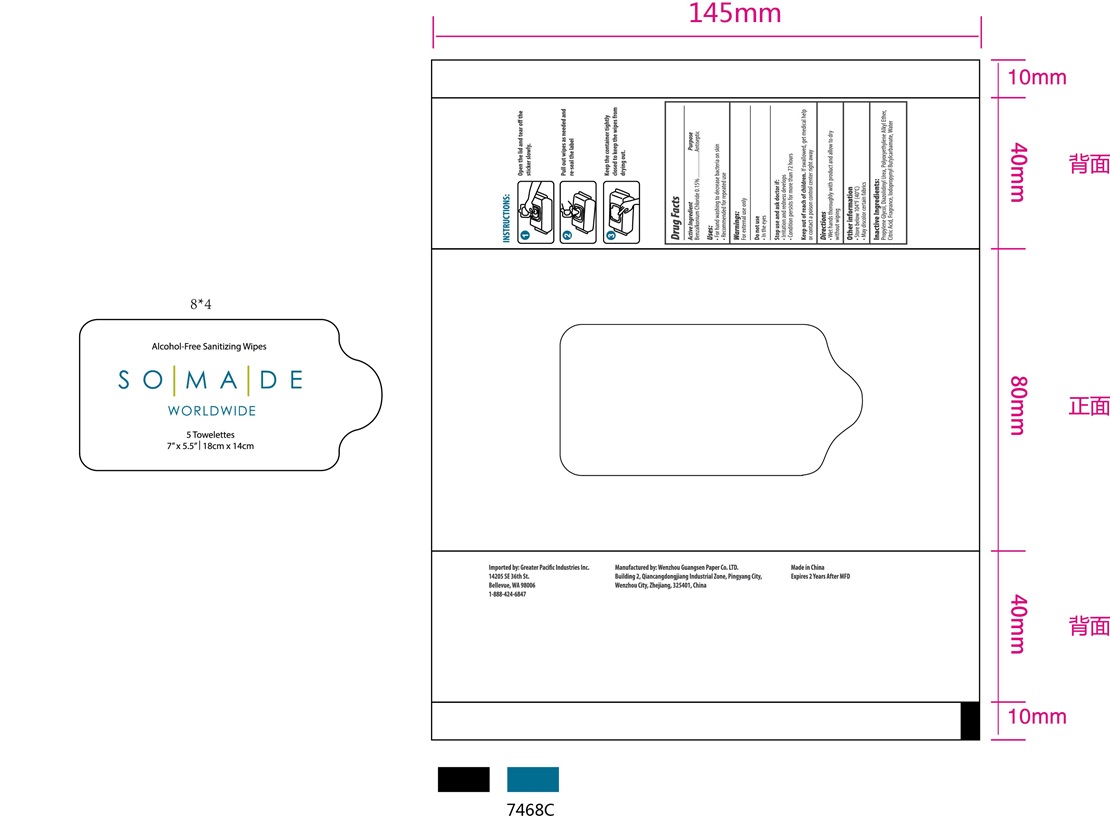 DRUG LABEL: sanitizing wipe
NDC: 78369-301 | Form: CLOTH
Manufacturer: WENZHOU GUANGSEN PAPER CO., LTD.
Category: otc | Type: HUMAN OTC DRUG LABEL
Date: 20200827

ACTIVE INGREDIENTS: BENZALKONIUM CHLORIDE 1 g/1 1
INACTIVE INGREDIENTS: FRAGRANCE LAVENDER & CHIA F-153480; BUTYL CARBAMATE; DIAZOLIDINYL UREA; WATER; C12-14 PARETH-3; PROPYLENE GLYCOL; CITRIC ACID MONOHYDRATE

sanitizing wipe

sanitizing wipe

Active Ingredient(s)

Benzalkonium Chloride 1g/pcs. Purpose: Antiseptic

Purpose

Antiseptic, sanitizing wipe

Use

sanitizing wipe to help reduce bacteria that potentially can cause disease. For use when soap and water are not available.

Warnings

For external use only. Flammable. Keep away from heat or flame

Do not use

- in children less than 2 months of age
- on open skin wounds

When using this product keep out of eyes, ears, and mouth. In case of contact with eyes, rinse eyes thoroughly with water.
Stop use and ask a doctor if irritation or rash occurs. These may be signs of a serious condition.
Keep out of reach of children. If swallowed, get medical help or contact a Poison Control Center right away.

Stop use and ask a doctor if irritation or rash occurs. These may be signs of a serious condition.

Keep out of reach of children. If swallowed, get medical help or contact a Poison Control Center right away.

Directions

- Wipe the surface of the skin and let it dry naturally.
- Supervise children under 6 years of age when using this product to avoid swallowing.

Other information

- Store between 15-30C (59-86F)
- Avoid freezing and excessive heat above 40C (104F)

Inactive ingredients

Lodopropynyl Butylcarbamate
Diazolidinyl Urea
Polyoxyethylene alkyl Ether
Propylene Glycol
Citric Acid
Fragrance
Water